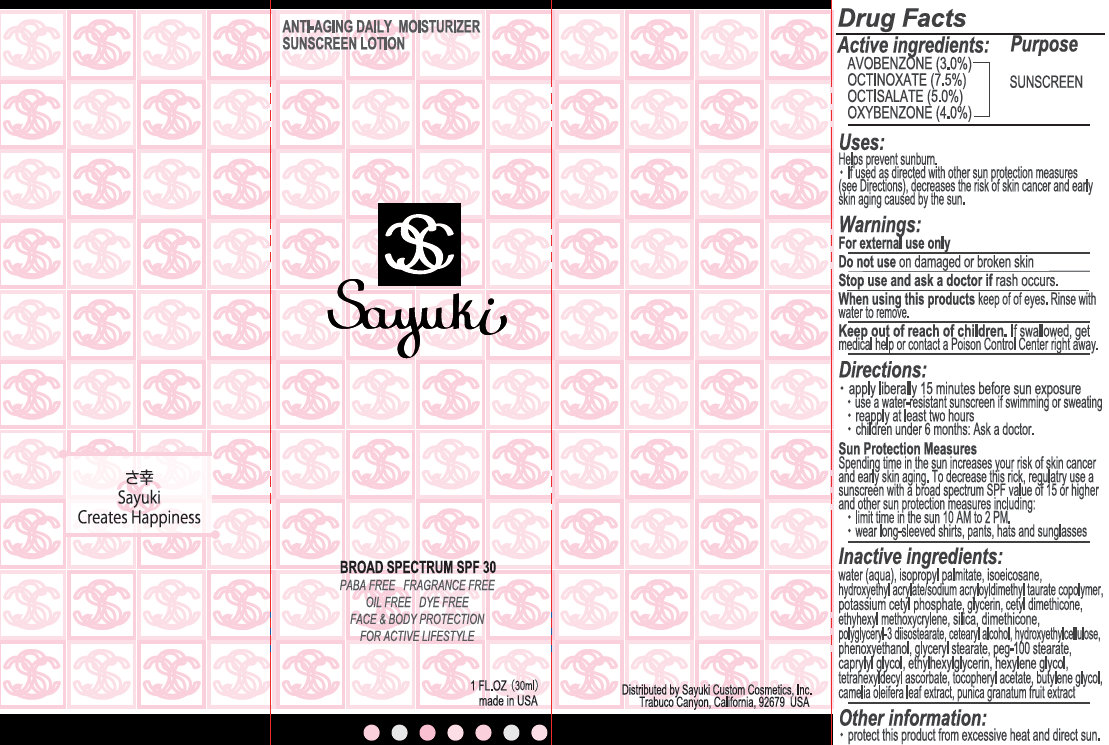 DRUG LABEL: Sayuki Broad Spectrum SPF 30 Anti-Aging Daily Moisturizer Sunscreen
NDC: 49517-0001 | Form: LOTION
Manufacturer: Sayuki Custom Cosmetics
Category: otc | Type: HUMAN OTC DRUG LABEL
Date: 20181129

ACTIVE INGREDIENTS: AVOBENZONE 30 mg/1 mL; OCTINOXATE 75 mg/1 mL; OCTISALATE 50 mg/1 mL; OXYBENZONE 40 mg/1 mL
INACTIVE INGREDIENTS: WATER; ISOPROPYL PALMITATE; ISOEICOSANE; SODIUM ACRYLATE/SODIUM ACRYLOYLDIMETHYLTAURATE COPOLYMER (4000000 MW); POTASSIUM CETYL PHOSPHATE; GLYCERIN; SILICON DIOXIDE; DIMETHICONE; POLYGLYCERYL-3 DIISOSTEARATE; CETOSTEARYL ALCOHOL; PHENOXYETHANOL; GLYCERYL MONOSTEARATE; PEG-100 STEARATE; CAPRYLYL GLYCOL; ETHYLHEXYLGLYCERIN; HEXYLENE GLYCOL; TETRAHEXYLDECYL ASCORBATE; .ALPHA.-TOCOPHEROL ACETATE; BUTYLENE GLYCOL; POMEGRANATE

Sayuki Broad Spectrum SPF 30 Anti-Aging Daily Moisturizer Sunscreen

Purpose

Sunscreen

Active ingredients:

AVOBENZONE (3.0%)
OCTINOXATE (7.5%)
OCTISALATE (5.0%)
OXYBENZONE (4.0%)

Uses:

- helps prevent sunburn
- if used as directed with other sun protection measure (see Directions), decrease the risk of skin cancer and early skin aging caused by the sun.

Warnings:

For external use only

Do not use

on damaged or broken skin.

Stop use and ask a doctor

if rash occurs.

When using this product

keep out of eyes. Rinse with water to remove.

Keep out of reach of children.

If swallowed, get medical help or contact a Poison Control Center right away.

Directions:

- apply liberally 15 minutes before sun exposure
- use a water-resistant sunscreen if swimming or sweating
- reapply at least every 2 hours
- children under 6 months: Ask a doctor

Sun Protection Measures

Spending time in the sun increases your risk of skin cancer and early skin aging. To decrease this risk, regularly use a sunscreen with a broad spectrum SPF value of 15 or higher and other sun protection measures including:

- limit time in the sun 10 AM to 2 PM
- wear long-sleeved shirts, pants, hats and sunglasses.

Inactive ingredients:

Water (Aqua), Isopropyl Palmitate, Isoeicosane, Hydroxyethyl Acrylate/Sodium Acryloyldimethyl Taurate Copolymer, Potassium Cetyl Phosphate, Glycerin, Cetyl Dimethicone, Ethyhexyl Methoxycrylene, Silica, Dimethicone, Polyglyceryl-3 Diisostearate, Cetearyl Alcohol, Hydroxyethylcellulose, Phenoxyethanol, Glyceryl Stearate, Peg-100 Stearate, Caprylyl Glycol, Ethylhexylglycerin, Hexylene Glycol, Tetrahexyldecyl Ascorbate, Tocopheryl Acetate, Butylene Glycol, Camelia Oleifera Leaf Extract, Punica Granatum Fruit Extract.

Other information:

- protect this product from excessive heat and direct sun.

PACKAGE LABEL

Sayuki Anti-Aging Daily Moisturizer Sunscreen Lotion BROAD SPECTRUM SPF 30 PABA FREE FRAGRANCE FREE OIL FREE DYE FREE FACE AND BODY PROTECTION FOR ACTIVE LIFESTYLE 1 FL. OZ (30ml) made in USA Distributed by Sayuki Custom Cosmetics, Inc. Trabuco Canyon, Californina, 92679 USA Sayuki Creates Happiness